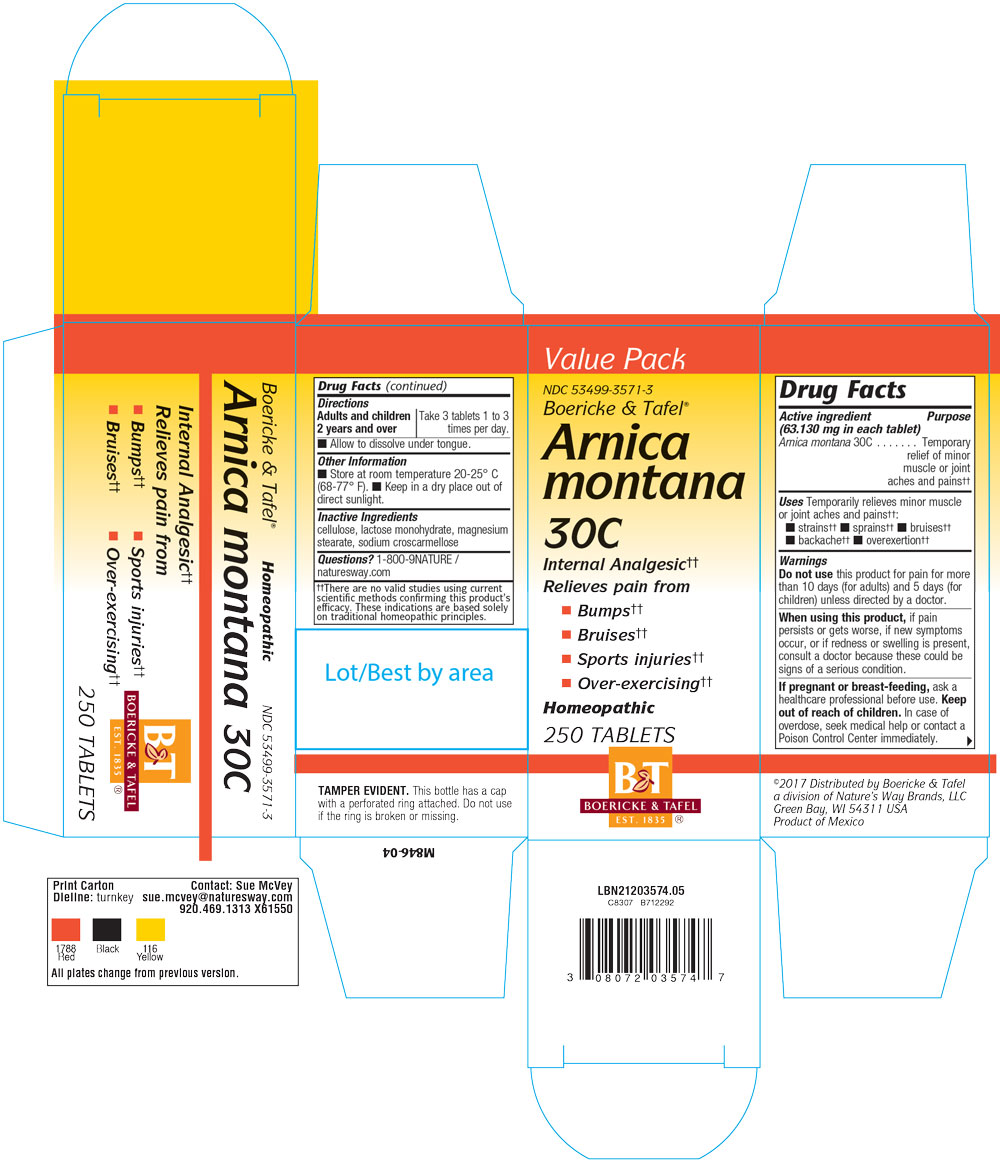 DRUG LABEL: Arnica Montana 30C
NDC: 68466-1041 | Form: TABLET
Manufacturer: Schwabe Mexico, S.A. de C.V.
Category: homeopathic | Type: HUMAN OTC DRUG LABEL
Date: 20220520

ACTIVE INGREDIENTS: ARNICA MONTANA 30 [hp_C]/1 1
INACTIVE INGREDIENTS: CELLULOSE, MICROCRYSTALLINE; LACTOSE MONOHYDRATE; MAGNESIUM STEARATE; CROSCARMELLOSE SODIUM

Arnica Montana 30C

Active Ingredient

Arnica Montana 30C

Inactive Ingredients

CELLULOSE

CROSCARMELLOSE SODIUM

LACTOSE MONOHYDRATE

MAGNESIUM STEARATE

Dosage & Administration

Directions: Adults or children over 2 years: Take 3 tablets 1-3 times a day.

Allow to dissolve under tongue.

Indications & Usage

Temporarily relieves minor muscle or joint aches and pains from strains, sprains, bruises, backache, over extertion.

Purpose

For the temporary relief of minor muscle or joint aches and pains from strains, sprains, bruises, backache and over exertion.

Warnings

Do not use this product for pain for more than 10 days (adult) or 5 days (children) unless directed by a doctor.

When using

When using this product, if pain persists or gets worse, if new symptoms occur, or if redness or swelling is present, consult a doctor because these could be signs of a serious condition.

Keep Out of Reach of Children

Overdosage

In case of overdose, seek medical help or contact a Poison Control Center immediately.